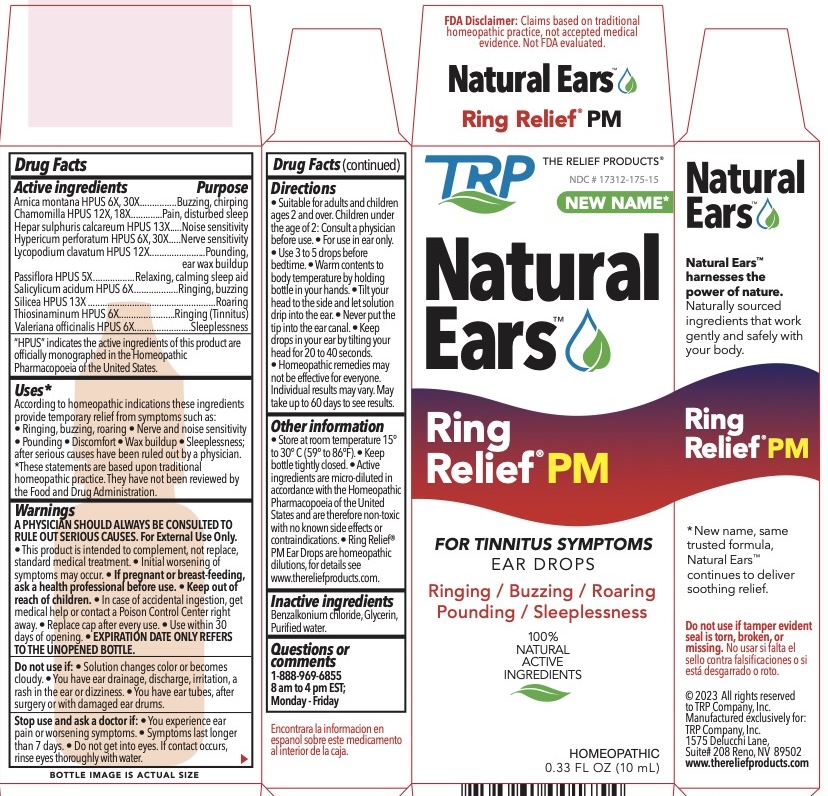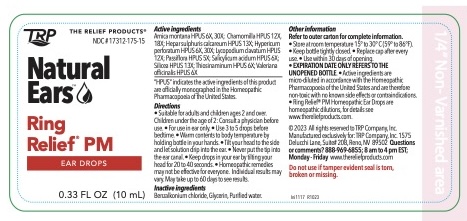 DRUG LABEL: Ring Relief PM Nighttime Formula
NDC: 17312-175 | Form: LIQUID
Manufacturer: TRP Company
Category: homeopathic | Type: HUMAN OTC DRUG LABEL
Date: 20251215

ACTIVE INGREDIENTS: ARNICA MONTANA 6 [hp_X]/1 mL; CALCIUM SULFIDE 13 [hp_X]/1 mL; HYPERICUM PERFORATUM 6 [hp_X]/1 mL; LYCOPODIUM CLAVATUM SPORE 12 [hp_X]/1 mL; MATRICARIA CHAMOMILLA 12 [hp_X]/1 mL; SALICYLIC ACID 6 [hp_X]/1 mL; SILICON DIOXIDE 13 [hp_X]/1 mL; VALERIAN 6 [hp_X]/1 mL; ALLYLTHIOUREA 6 [hp_X]/1 mL; PASSIFLORA INCARNATA FLOWER 5 [hp_X]/1 mL
INACTIVE INGREDIENTS: GLYCERIN; BENZALKONIUM CHLORIDE; WATER

Ring Relief ® PM Nighttime Formula Ear Drops

ACTIVE INGREDIENT

Arnica montana HPUS 6X, 30X................Buzzing, chirping
Chamomilla HPUS 12X, 18X....................Pain, disturbed sleep
Hepar sulphuris calcareum HPUS 13X....Noise sensitivity
Hypericum perforatum HPUS 6X, 30X.....Nerve sensitivity
Lycopodium clavatum HPUS 12X............Pounding, ear wax buildup
Passiflora HPUS 5X.................................Relaxing, calming sleep aid
Salicylicum acidum HPUS 6X..................Ringing, buzzing
Silicea HPUS 13X....................................Roaring
Thiosinaminum HPUS 6X........................Ringing (Tinnitus)
Valeriana officinalis HPUS 6X..................Sleeplessness

"HPUS" indicates the active ingredients are in the Homeopathic Pharmacopoeia of the United States.

PURPOSE

Arnica montana HPUS- Buzzing, chirping
Chamomilla HPUS - Pain, disturbed sleep
Hepar sulphuris calcareum HPUS - Noise sensitivity
Hypericum perforatum HPUS - Nerve sensitivity
Lycopodium clavatum HPUS - Pounding, ear wax buildup
Passiflora HPUS - Relaxing, calming sleep aid
Salicylicum acidum HPUS - Ringing, buzzing
Silicea HPUS - Roaring
Thiosinaminum HPUS - Ringing (Tinnitus)
Valeriana officinalis HPUS - Sleeplessness

Uses:*
According to homeopathic indications these ingredients provide temporary relief from symptoms such as: • Ringing, buzzing, roaring • Nerve and noise sensitivity • Pounding • Discomfort • Wax buildup • Sleeplessness; after serious causes have been ruled out by a physician.
*These statements are based upon traditional homeopathic practice. They have not been reviewed by the Food and Drug Administration.

Warnings:

A PHYSICIAN SHOULD ALWAYS BE CONSULTED TO RULE OUT SERIOUS CAUSES. For External Use Only.

- This product is intended to complement, not replace, standard medical treatment.
- Initial worsening of symptoms may occur.

Do not get into eyes. If contact occurs, rinse eyes thoroughly with water.

PREGNANCY OR BREAST FEEDING

If pregnant or breast-feeding, ask a health professional before use.

Do not use:

- If solution changes color or becomes cloudy.
- If you have ear drainage, discharge, irritation, a rash in the ear or dizziness.
- If you have ear tubes, after surgery or with damaged ear drums.

Keep out of reach of children

In case of accidental ingestion, get medical help or contact a Poison Control Center right away.

Directions:
• Suitable for adults and children ages 2 and over. Children under the age of 2: Consult a physician before use. • For use in ear only. • Use 3 to 5 drops before bedtime. • Warm contents to body temperature by holding bottle in your hands. • Tilt your head to the side and let solution drip into the ear. • Never put the tip into the ear canal. • Keep drops in your ear by tilting your head for 20 to 40 seconds. • Homeopathic remedies may not be effective for everyone. Individual results may vary. May take up to 60 days to see results.

Other information:

• Store at room temperature 15° to 30° C (59° to 86°F). • Keep bottle tightly closed. • Active ingredients are micro-diluted in accordance with the Homeopathic Pharmacopoeia of the United States and are therefore non-toxic with no known side effects or contraindications. • Ring Relief® PM Ear Drops are homeopathic dilutions, for details see www.thereliefproducts.com.

Inactive Ingredients:
Benzalkonium Chloride, Glycerin, Purified Water.

Questions or comments?

www.thereliefproducts.com, 1-888-969-6855

Stop Use

Stop use and ask a doctor if: • You experience ear pain or worsening symptoms. • Your symptoms last longer than 7 days

PACKAGE LABEL

FDA Disclaimer: Claims based on traditional homeopathic practice, not accepted medical evidence. Not FDA evaluated.